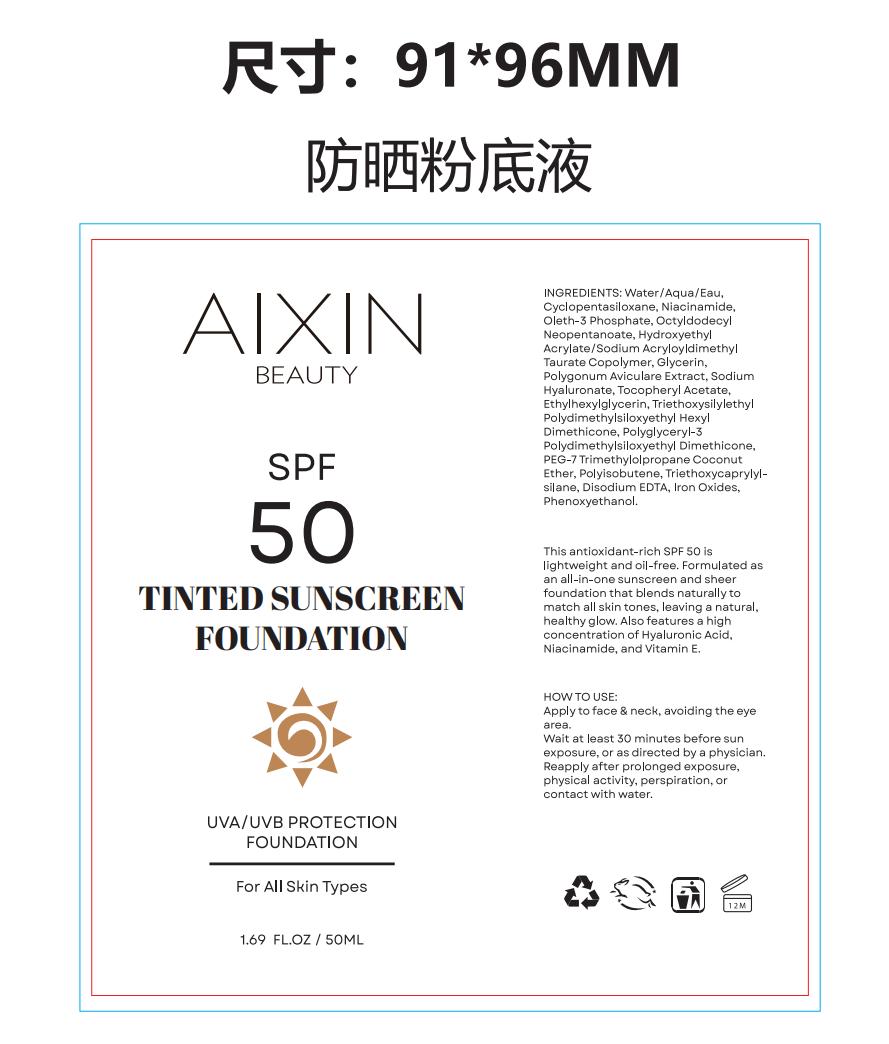 DRUG LABEL: TINTED SUNSCREEN FOUNDATION
NDC: 85897-876 | Form: LIQUID
Manufacturer: Guanghzou AiXin Biotech Co Ltd
Category: homeopathic | Type: HUMAN OTC DRUG LABEL
Date: 20250707

ACTIVE INGREDIENTS: ZINC OXIDE 8 g/1 1; WATER 35 g/1 1
INACTIVE INGREDIENTS: TITANIUM DIOXIDE; ALOE BARBADENSIS LEAF; HYDROLYZED WHEAT PROTEIN (ENZYMATIC, 3000 MW); CUCUMIS SATIVUS (CUCUMBER) SEED; DAUCUS CAROTA SATIVA (CARROT) JUICE; AGAVE TEQUILANA LEAF; CAPRYLIC/CAPRIC TRIGLYCERIDE; CARTHAMUS TINCTORIUS (SAFFLOWER) OLEOSOMES; CETEARYL ALCOHOL; COCO-GLUCOSIDE; TOCOPHEROL; NIACINAMIDE; ETHYLHEXYLGLYCERIN; MALTOSE; SODIUM HYALURONATE; GLYCERIN; HYDROLYZED JOJOBA ESTERS

ACTIVE INGREDIENT

Water,Zinc Oxide

PURPOSE

Sun protection

KEEP OUT OF REACH OF CHILDREN SECTION

Keep out of reach of children

INACTIVE INGREDIENT

Titanium Dioxide,Agave Tequilana Leaf Extract,Aloe Barbadensis Extract,Cucumis Sativus (Cucumber) Fruit Extract

Sativa (Carrot) Extract,Caprylic/Capric Triglyceride,Carthamus Tinctorius (Saflower) Oleosomes,Rose Damascena (Rose) Exract

Cetearyl Alcohol,Coco-glucoside,Glycerin,Hydrolyzed Wheat Protein,Iron Oxides,Jojoba Esters,Maltose

Sodium Hyaluronate,Tocopherol,Niacinamide,Ethylhexylglycerin

DOSAGE AND ADMINISTRATION

1.69 FL.OZ/50 ML

INDICATIONS AND USAGE

Sun protection